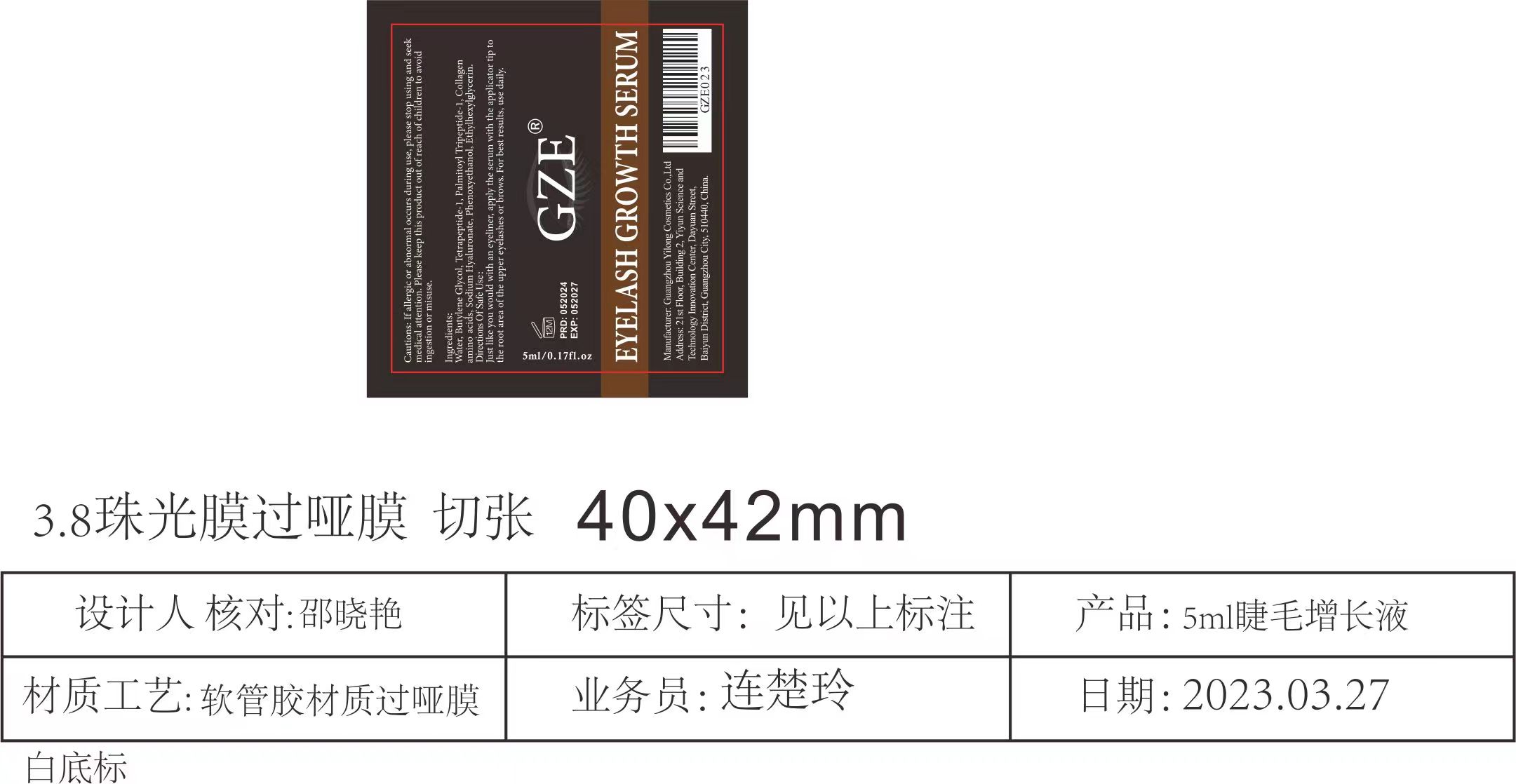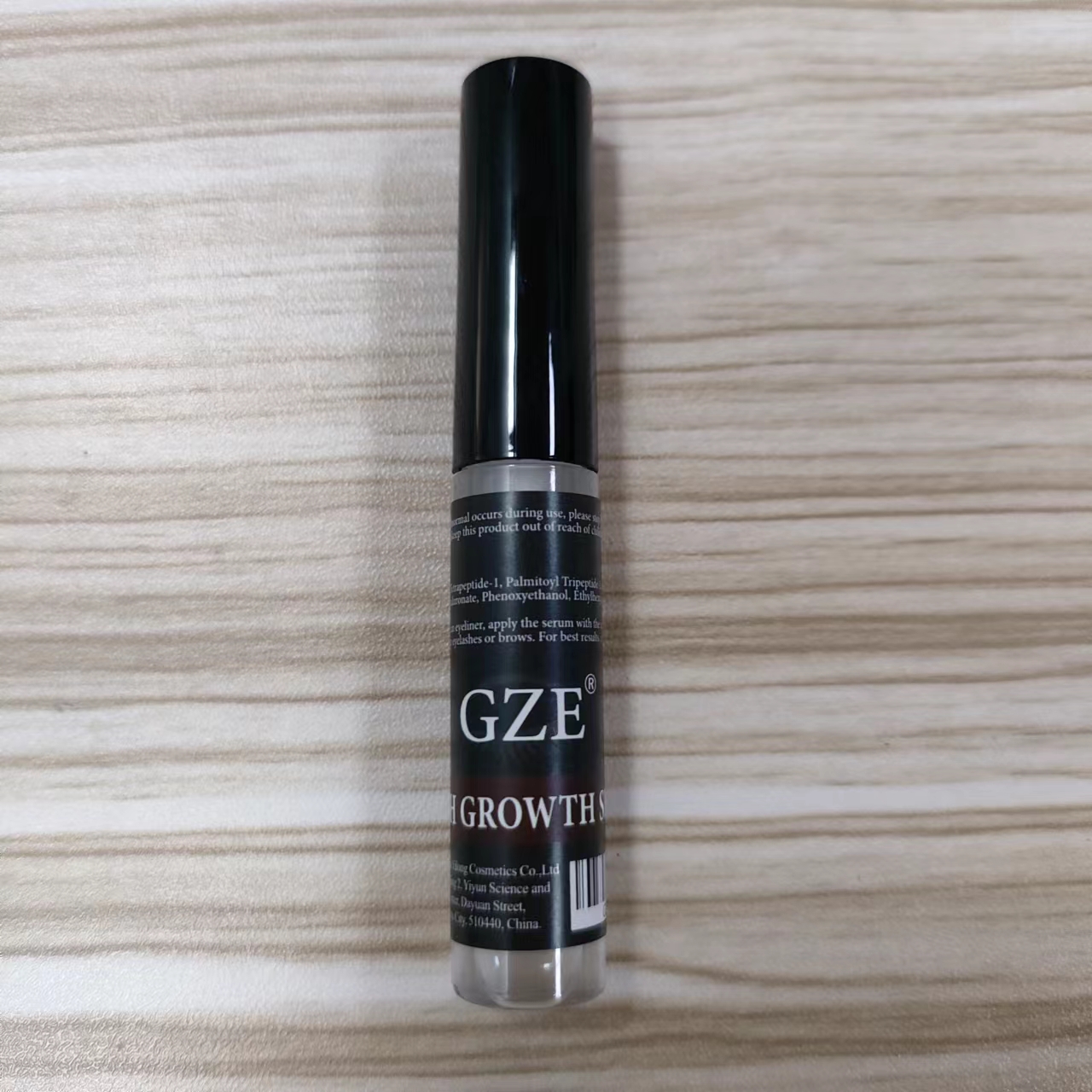 DRUG LABEL: GZE EYELASH GROWTH  SERUM
NDC: 83566-023 | Form: LIQUID
Manufacturer: Guangzhou Yilong Cosmetics Co., Ltd
Category: otc | Type: HUMAN OTC DRUG LABEL
Date: 20240708

ACTIVE INGREDIENTS: TETRAPEPTIDE-1 5 g/100 mL; PALMITOYL TRIPEPTIDE-1 5 g/100 mL
INACTIVE INGREDIENTS: ETHYLHEXYLGLYCERIN; AMINO ACIDS; PHENOXYETHANOL; WATER; BUTYLENE GLYCOL; PEG-9 DIGLYCIDYL ETHER/SODIUM HYALURONATE CROSSPOLYMER

ACTIVE INGREDIENT

Tetrapeptide-1

Palmitoyl Tripeptide-1

INACTIVE INGREDIENT

Water

Butylene Glycol

Collagen amino acids

Sodium Hyaluronate

Phenoxyethanol

Ethylhexylglycerin

PURPOSE

Eyelash growth

INDICATIONS AND USAGE

Just like you would with an eyeliner, apply the serum with the applicator tip to the root area of the upper eyelashes or brows. For best results, use daily.

WARNINGS

For external use only.

Stop use and ask a doctor if rash occurs.

Do not use on damaged or broken skin.

When using this product keep out of eyes. Rinse with water to remove.

Keep out of reach of children. If swallowed, get medical help or contact a Poison Control Center right away.

DOSAGE AND ADMINISTRATION

Just like you would with an eyeliner, apply the serum with the applicator tip to the root area of the upper eyelashes or brows. For best results, use daily.